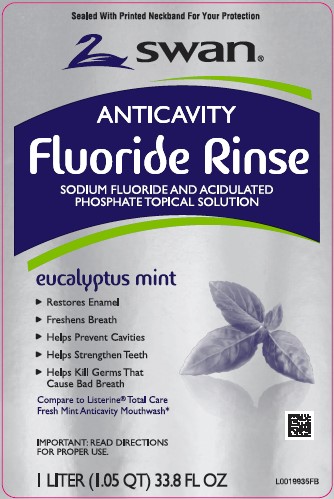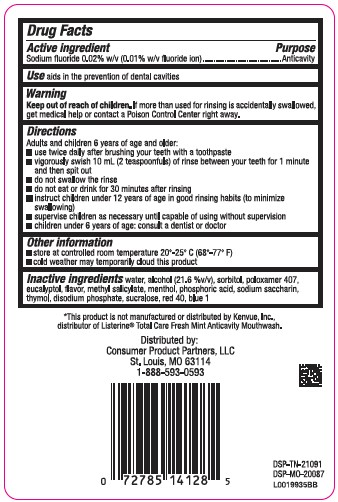 DRUG LABEL: Anticavity Fluoride Rinse
NDC: 11344-163 | Form: MOUTHWASH
Manufacturer: Consumer Product Partners, LLC
Category: otc | Type: HUMAN OTC DRUG LABEL
Date: 20250716

ACTIVE INGREDIENTS: SODIUM FLUORIDE 0.1 mg/1 mL
INACTIVE INGREDIENTS: WATER; ALCOHOL; SORBITOL; POLOXAMER 407; EUCALYPTOL; METHYL SALICYLATE; MENTHOL; PHOSPHORIC ACID; SACCHARIN; THYMOL; SODIUM PHOSPHATE, DIBASIC; SUCRALOSE; FD&C RED NO. 40; FD&C BLUE NO. 1

Swan 163.005/163AF-AG
Anticavity Fluoride Rinse Mint

Active ingredient

Sodium fluoride 0.02% (0.01% Fluoride ion)

Purpose

Anticavity

Use

aids in the prevention of dental cavities

Warnings

for this product

Keep out of reach of children.

If more than used for rinsing is accidentally swallowed, get medical help or contact a Poison Control Center right away.

Directions

Adults and children 6 years of age and older:

- use twice daily after brushing your teeth with a toothpaste
- vigorously swish 10 mL (2 teaspoonfuls) of rinse between your teeth for 1 minute and then spit out
- do not swallow the rinse
- do not eat or drink for 30 minutes after rinsing
- instruct children under 12 years of age in good rinsing habits (to minimize swallowing)
- supervise children as necessary until capable of using without supervision
- children under 6 years of age: consult a dentist or doctor

Other information

- store at controlled room temperature 20⁰ - 25⁰C (68⁰ - 77⁰F)
- cold weather may temporarily cloud this product

Inactive ingredients

water, alcohol (21.6 %v/v), sorbitol, poloxamer 407, eucalyptol, flavor, methyl salicylate, menthol, phosphoric acid, sodium saccharin, thymol, disodium phosphate, sucralose, red 40, blue 1

Disclaimer

*This product is not manufactured or distributed by Kenvue, Inc., distributor of Listerine® Total Care Fresh Mint Anticavity Mouthwash.

Adverse reactions

Distributed by:

Consumer Product Partners, LLC

St. Louis, MO 63114

1-888-593-0593

DSP-TN-21091

DSP-MO-20087

Principal display panel

Sealed With Printed Neckband For Your Protection

Swan®

ANTICAVITY

Fluoride Rinse

SODIUM FLUORIDE AND ACIDULATED PHOSPHATE TOPICAL SOLUTION

eucalyptus mint

- Restores Enamel
- Freshens Breath
- Helps Prevent Cavities
- Helps Strengthen Teeth
- Helps Kill Germs That Cause Bad Breath

Compare Listerine® Total Care Fresh Mint Anticavity Mouthwash*

IMPORTANT: READ DIRECTIONS FOR PROPER USE

1 LITER (1.05 QT) 33.8 FL OZ